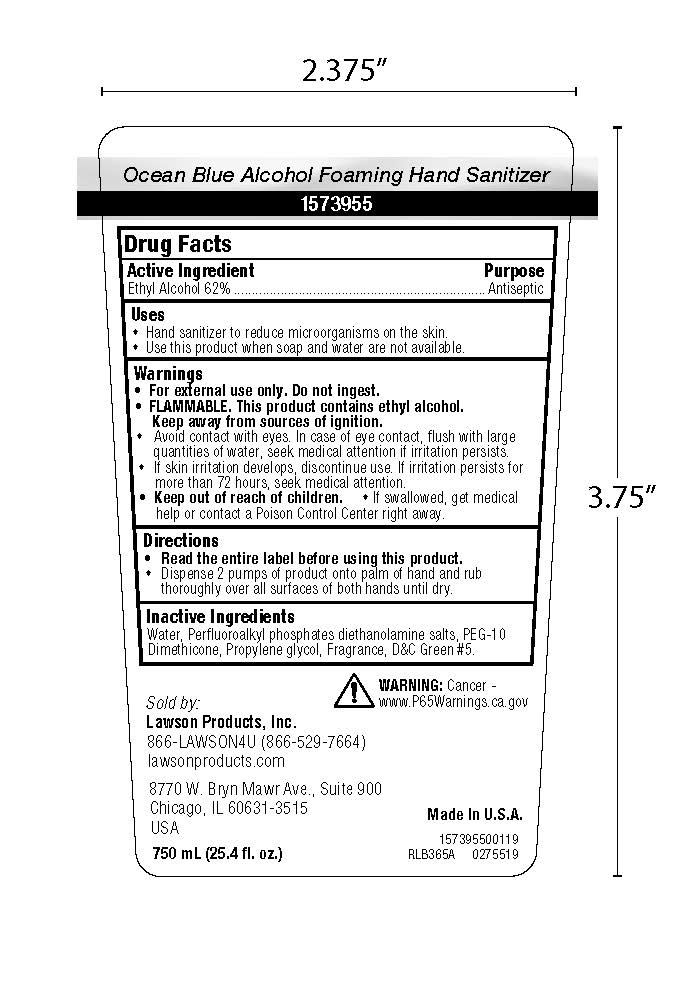 DRUG LABEL: Alcohol Foaming Hand Sanitizer
NDC: 62428-701 | Form: SOAP
Manufacturer: Lawson Prodcuts, Inc
Category: otc | Type: HUMAN OTC DRUG LABEL
Date: 20190314

ACTIVE INGREDIENTS: ALCOHOL 0.62 mL/1 mL
INACTIVE INGREDIENTS: D&C GREEN NO. 5; PROPYLENE GLYCOL; C20-22 ALKYL PHOSPHATE; WATER; PEG-10 DIMETHICONE (600 CST)

Ocean Blue Alcohol Foaming Hand Sanitizer

Active Ingredient

Ethyk Alcohol 62%

Warnings

For external use only. Do not ingest.
FLAMMABLE. This product contains ethyl alcohol. Keep away from sources of ignition.
Avoid contact with eyes. In case of eye contact, flush with large quantities of water, seek medical attention if irritation persists.
If skin irritation develops, discontinue use. If irritation persists for more than 72 hours, seek medical attention.
Keep out of reach of children.
If swallowed, get medical help or contact a Poison Control Center right away.

Inactive Ingredients

Water, Propylene Glycol, Acrylic Polymer, Alkyl Phosphate Salts, Fragrance, DC Green #5.

Purpose

Antiseptic

Alcohol Foaming Hand Sanitizer

KEEP OUT OF REACH OF CHILDREN

Directions

Read the entire label before using this product.

Dispense 2 pumps of product onto palm of hand and rub thoroughly over all surfaces of both hands until dry.

Uses

Use hand sanitizer to reduce microorganisms on the skin.
Use this product when soap and water are not available.